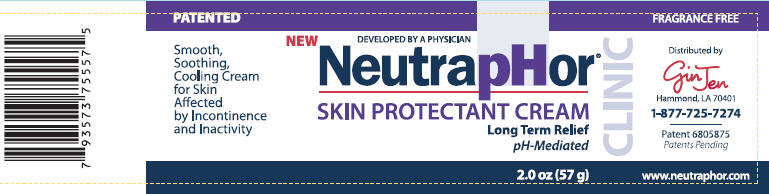 DRUG LABEL: NeutrapHor 
NDC: 50952-002 | Form: CREAM
Manufacturer: pH R&D LLC
Category: otc | Type: HUMAN OTC DRUG LABEL
Date: 20101119

ACTIVE INGREDIENTS: Dimethicone 0.57 g/57 g
INACTIVE INGREDIENTS: Water; Mineral Oil; Petrolatum; Sorbitan Sesquioleate; Sorbitol; Lanolin Alcohols; Aluminum Hydroxide; Magnesium Hydroxide; Butylated Hydroxytoluene; Ethylhexylglycerin; Phenoxyethanol

NeutrapHor®
SKIN PROTECTANT CREAM

Drug Facts

Active Ingredient

Dimethicone 1%

Purpose

Skin protectant

Uses

- temporarily protects and helps relieve chapped or cracked skin
- temporarily protects minor
  - cuts
  - scrapes
  - burns

Warnings

For external use only

When Using This Product

- Keep out of eyes. Rinse eyes thoroughly with water to remove.

Stop Use And Ask A Doctor If

- condition worsens
- symptoms last more than 7 days or clear up and occur again within a few days

Do Not Use On

- deep or puncture wounds
- animal bites
- serious burns

Keep Out Of Reach Of Children

- If swallowed, get medical help or contact a Poison Control Center right away

Directions

Apply cream liberally as often as needed

Inactive Ingredients

Water, Mineral Oil, White Petrolatum, Ceresin, Sorbitan Sesquioleate, Sorbitol, Lanolin Alcohol, Aluminum Hydroxide, Magnesium Hydroxide, BHT Ethylhexylglycerin, Phenoxyethanol

Questions?

9a-5p weekdays M-F CST 1-877-725-7274

Distributed by
GinJen
Hammond, LA 70401

PRINCIPAL DISPLAY PANEL - 57 g jar label

PATENTED

Smooth,
Soothing,
Cooling Cream
for Skin
Affected
by Incontinence
and Inactivity

NEW

DEVELOPED BY A PHYSICIAN
NeutrapHor®
SKIN PROTECTANT CREAM
Long Term Relief
pH-Mediated

CLINIC

FRAGRANCE FREE

Distributed by
GinJen
Hammond, LA 70401
1-877-725-7274

Patent 6805875
Patents Pending

2.0 oz (57 g)
www.neutraphor.com